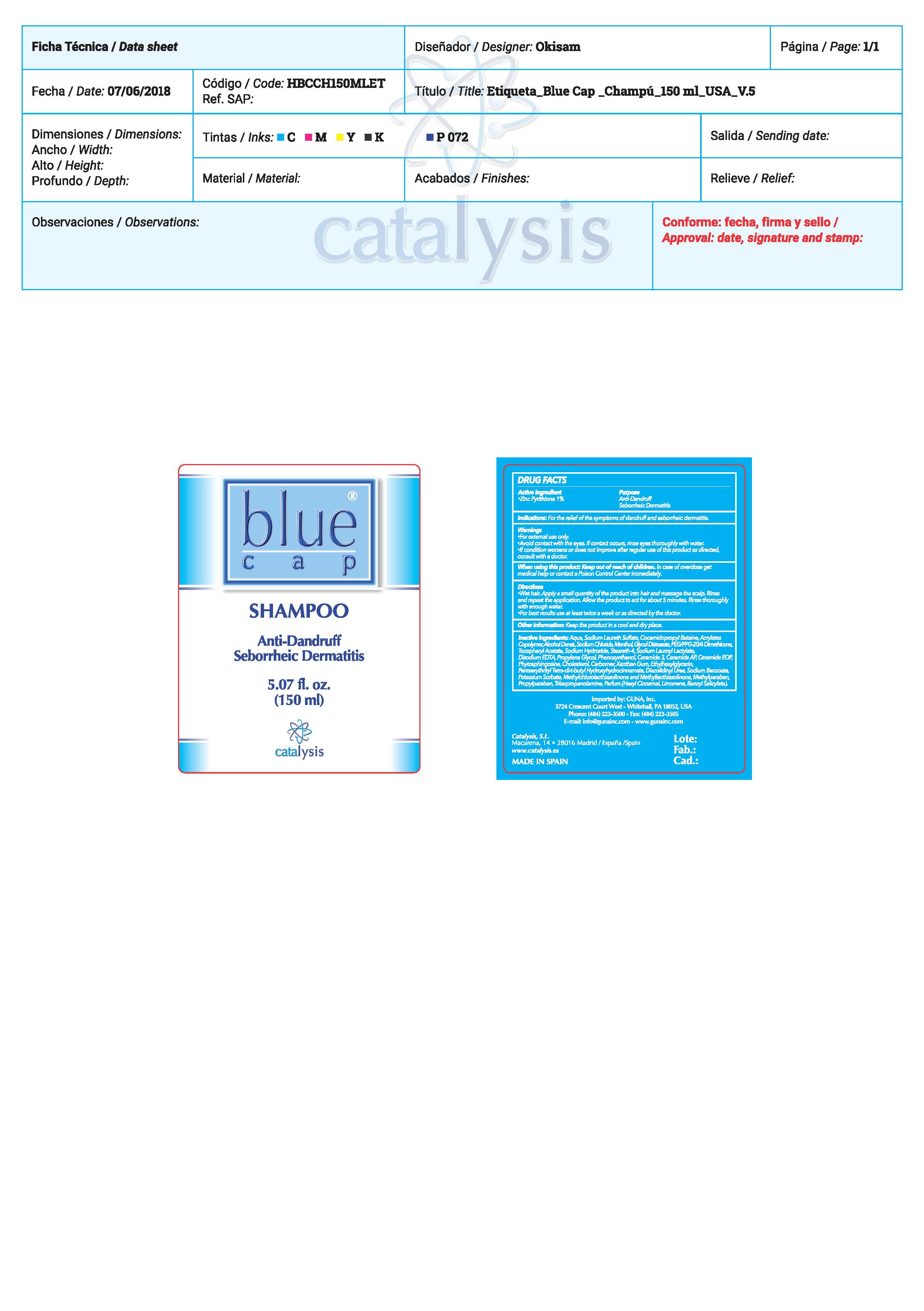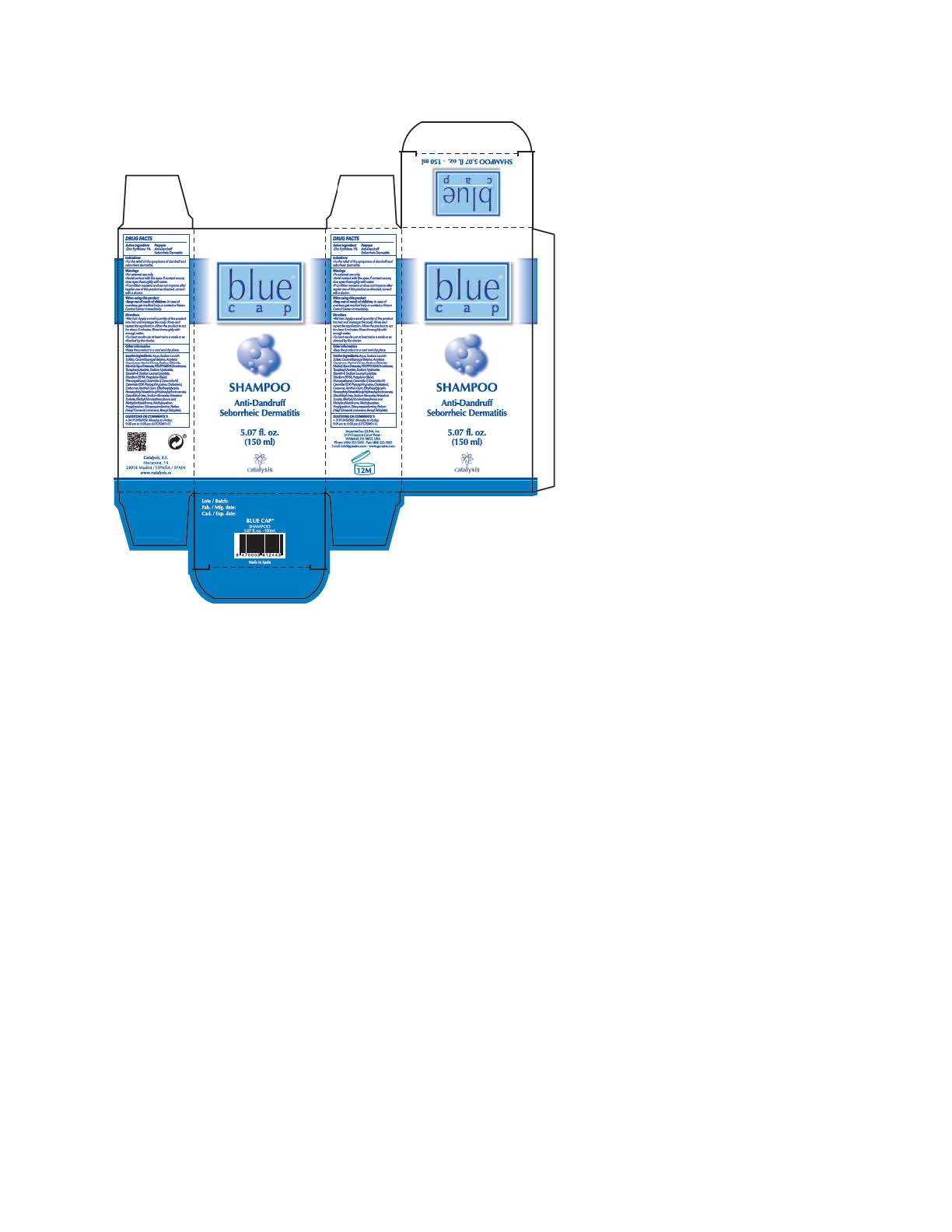 DRUG LABEL: Blue Cap
NDC: 64539-020 | Form: SHAMPOO
Manufacturer: Catalysis, SL
Category: otc | Type: HUMAN OTC DRUG LABEL
Date: 20180913

ACTIVE INGREDIENTS: PYRITHIONE ZINC 1 mg/1 mL
INACTIVE INGREDIENTS: PROPANEDIOL; DIAZOLIDINYL UREA; CERAMIDE AP; WATER; SODIUM LAURYL SULFATE; METHACRYLIC ACID - ETHYL ACRYLATE COPOLYMER (1:2); SODIUM LAUROYL LACTYLATE; ALCOHOL; SODIUM CHLORIDE; MENTHOL; GLYCOL DISTEARATE; PEG/PPG-20/6 DIMETHICONE; .ALPHA.-TOCOPHEROL ACETATE; SODIUM HYDROXIDE; STEARETH-4; EDETATE DISODIUM; PHENOXYETHANOL; CARBOXYPOLYMETHYLENE; ETHYLHEXYLGLYCERIN; PENTAERYTHRITOL TETRAKIS(3-(3,5-DI-TERT-BUTYL-4-HYDROXYPHENYL)PROPIONATE); SODIUM BENZOATE; POTASSIUM SORBATE; METHYLCHLOROISOTHIAZOLINONE; CERAMIDE 3; PHYTOSPHINGOSINE; CHOLESTEROL; XANTHAN GUM; METHYLISOTHIAZOLINONE; METHYLPARABEN; PROPYLPARABEN; TRIISOPROPANOLAMINE; .ALPHA.-HEXYLCINNAMALDEHYDE; BENZYL SALICYLATE; LIMONENE, (+)-; CERAMIDE 1; COCAMIDOPROPYL BETAINE

Blue Cap Shampoo

ACTIVE INGREDIENTS PURPOSE

Pyrithione Zinc 1%.................. Anti dandruff/ Seborrheic Dermatitis

Warnings

- For external use only.
- Avoid contact with the eyes. If contact occurs rinse the eyes throughly with water
- If conditions worsens or does not improves after regular use of this product as directed, consult with a doctor
- When using this product
- KEEP out of the reach of children. In case of overdose get medical help or contact the Poison Control Center inmediately.

WARNINGS

- For external use only.
- Avoid contact with the eyes. If contact occurs rinse the eyes throughly with water
- If conditions worsens or does not improves after regular use of this product as directed, consult with a doctor
- When using this product
- KEEP out of the reach of children. In case of overdose get medical help or contact the Poison Control Center inmediately.

Warnings

Keep out of reach of children

Questions or comments?

+ 34 91 345 6902 M-F 9:00 am to 5:00 pm

Other Information

. keep the product in a cool and dry place

Directions

- Wet hair. Apply a small amount quantity of the product into hair and massage the scalp. Rinse and repeat the application. Allow the product to act for 5 minutes. Rinse throughly with enough water.
- For best results use at least twice a week or as directed by the doctor

DOSAGE AND ADMINISTRATION

- Wet hair. Apply a small amount quantity of the product into hair and massage the scalp. Rinse and repeat the application. Allow the product to act for 5 minutes. Rinse throughly with enough water.
- For best results use at least twice a week or as directed by the doctor

Uses

- For the relief of the symptons of dandruff and seborrheic dermatitis

Inactive Ingredients

Water, Sodium Laureth Sulfate, Cocamidopropyl Betaine, Acrylates Copolymer, Zinc Pyrithione, Alcohol Denat, Sodium Chloride, Menthol, Glycol Distearate, PEG/PPG-20/6 Dimethicone, Tocopheryl Acetate, Sodium Hydroxide, Steareth-4, Sodium Lauroyl Lactylate, Disodium EDTA, Propylene Glycol, Phenoxyethanol, Ceramide 3, Ceramide AP, Ceramide EOP, Phytosphingosine, Cholesterol, Carbomer, Xanthan Gum, Ethylhexylglycerin, Pentaerythrityl Tetra-di-t-butyl Hydroxyhydrocinnamate, Diazolidinyl Urea, Sodium Benzoate, Potassium Sorbate, Methylchloroisothiazolinone, Methylisothiazolinone, Methylparaben, Propylparaben, Triisopropanolamine, Hexyl Cinnamal, Limonene, Benzyl Salicylate

Uses

- For the relief of the symptons of dandruff and seborrheic dermatitis